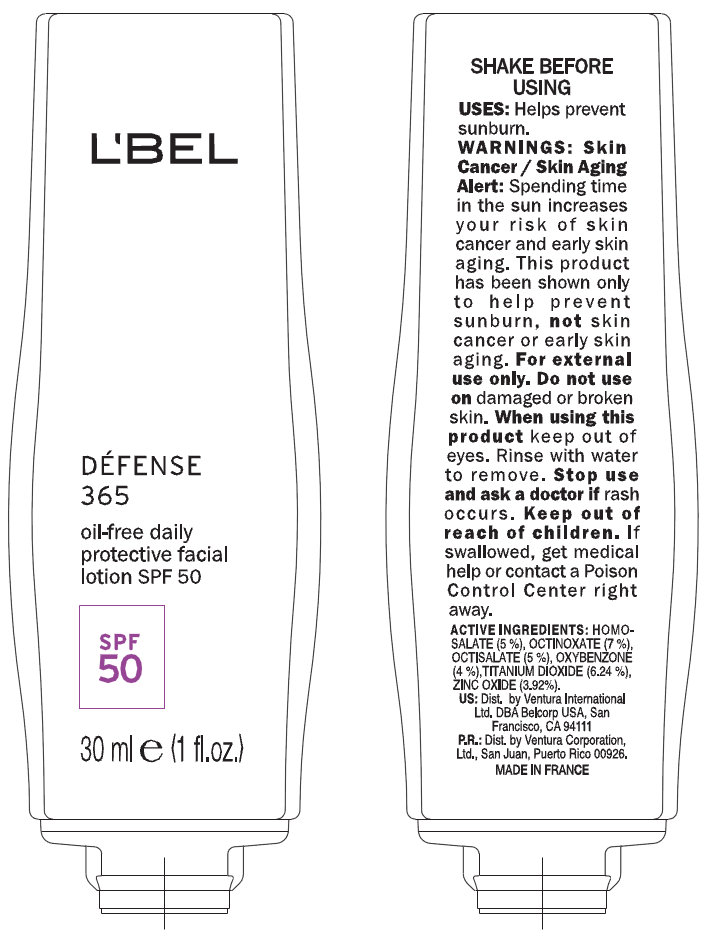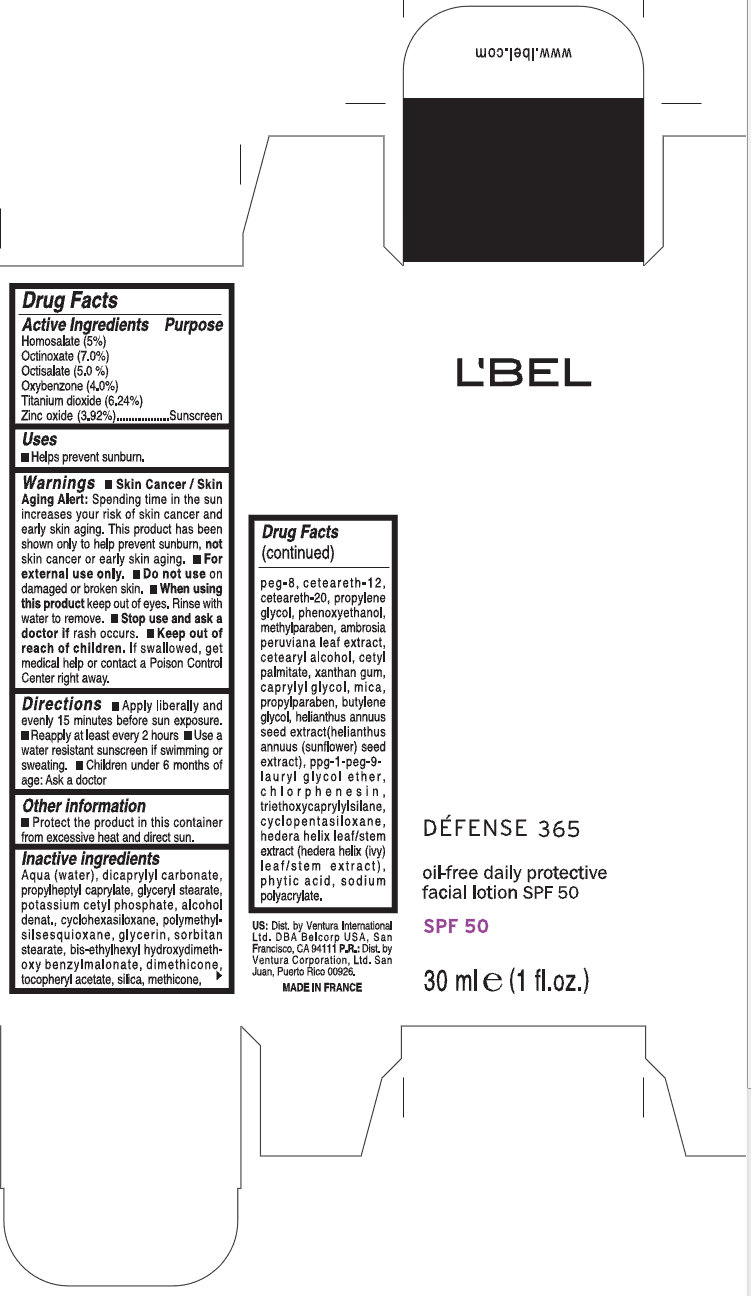 DRUG LABEL: LBEL DEFENSE 365 Daily Protective Facial SPF 50
NDC: 43455-0001 | Form: LOTION
Manufacturer: Ventura International, LTD
Category: otc | Type: HUMAN OTC DRUG LABEL
Date: 20120328

ACTIVE INGREDIENTS: HOMOSALATE 5 mL/100 mL; OCTINOXATE 7 mL/100 mL; OCTISALATE 5 mL/100 mL; OXYBENZONE 4 mL/100 mL; TITANIUM DIOXIDE 6.24 mL/100 mL; ZINC OXIDE 3.92 mL/100 mL
INACTIVE INGREDIENTS: WATER; DICAPRYLYL CARBONATE; PROPYLHEPTYL CAPRYLATE; GLYCERYL MONOSTEARATE; POTASSIUM CETYL PHOSPHATE; ALCOHOL; CYCLOMETHICONE 6; GLYCERIN; SORBITAN MONOSTEARATE; DIMETHICONE; .ALPHA.-TOCOPHEROL ACETATE; SILICON DIOXIDE; POLYETHYLENE GLYCOL 400; CETEARETH-12; POLYOXYL 20 CETOSTEARYL ETHER; PROPYLENE GLYCOL; METHYLPARABEN; AMBROSIA PERUVIANA LEAF; CETOSTEARYL ALCOHOL; CETYL PALMITATE; XANTHAN GUM; CAPRYLYL GLYCOL; MICA; PROPYLPARABEN; BUTYLENE GLYCOL; HELIANTHUS ANNUUS SEED WAX; CHLORPHENESIN; TRIETHOXYCAPRYLYLSILANE; CYCLOMETHICONE 5; HEDERA HELIX LEAF; FYTIC ACID; SODIUM POLYACRYLATE (8000 MW)

L'BEL DEFENSE 365 Oil-Free Daily Protective Facial Lotion SPF 50

Active Ingredients

Homosalate (5%)
Octinoxate (7.0%)
Octisalate (5.0%)
Oxybenzone (4.0%)
Titanium Dioxide (6.24%)
Zinc Oxide (3.92%)

Uses

- Helps prevent sunburn.

Warnings

- Skin Cancer / Skin Aging Alert: Spending time in the sun increases your risk of skin cancer and early skin aging. This product has been shown only to help prevent sunburn, not skin cancer or early skin aging.
- For external use only.

Do not use

on damaged or broken skin.

When using this product

keep out of eyes. Rinse with water to remove.

Stop use and ask a doctor

if rash occurs.

Keep out of reach of children

If swallowed, get medical help or contact a Poison Control Center right away.

Directions

- Apply liberally and evenly 15 minutes before sun exposure.
- Reapply at least every 2 hours
- Use a water resistant sunscreen if swimming or sweating.
- Children under 6 months of age: Ask a doctor.

Other Information

- Protect the product in this container from excessive heat and direct sun.

Inactive ingredients

Aqua (Water), dicaprylyl carbonate, propylheptyl caprylate, glyceryl stearate, potassium cetyl phosphate, alcohol denat., cyclohexasiloxane, polymethylsilsesquioxane, glycerin, sorbitan stearate, bis0ethylhexyl hydroxydimethoxy benzylmalonate, dimethicone, tocopheryl acetate, silica, methicone, peg-8, ceteareth-12, ceteareth-20, propylene glycol, phenoxyethanol, methylparaben, ambrosia peruviana leaf extract, cetearyl alcohol, cetyl palmitate, xanthan gum, caprylyl glycol, mica, propylparaben, butylene glycol, helianthus annuus seed extract (helianthus annuus (sunflower) seed extract), ppg-1-peg-9-lauryl glycol ether, chlorophenesin, triethoxycaprylylsilane, cyclopentasiloxane, hedera helix leaf/stem extract (hedera helix (ivy) leaf/stem extract), phytic acid, sodium polyacrylate.

Purpose

Sunscreen

PACKAGE LABEL

L'BEL DEFENSE 365 oil-free protective facial lotion SPF 50 30ml e (1 fl. oz.)
US: Dist. by Ventural Internationa Ltd. DBA Bellcorp USA, San Francisco, CA 94111
P.R. Dist. by Ventura Corporation Ltd., San Juan, Puerto Rico 00926 MADE IN FRANCE